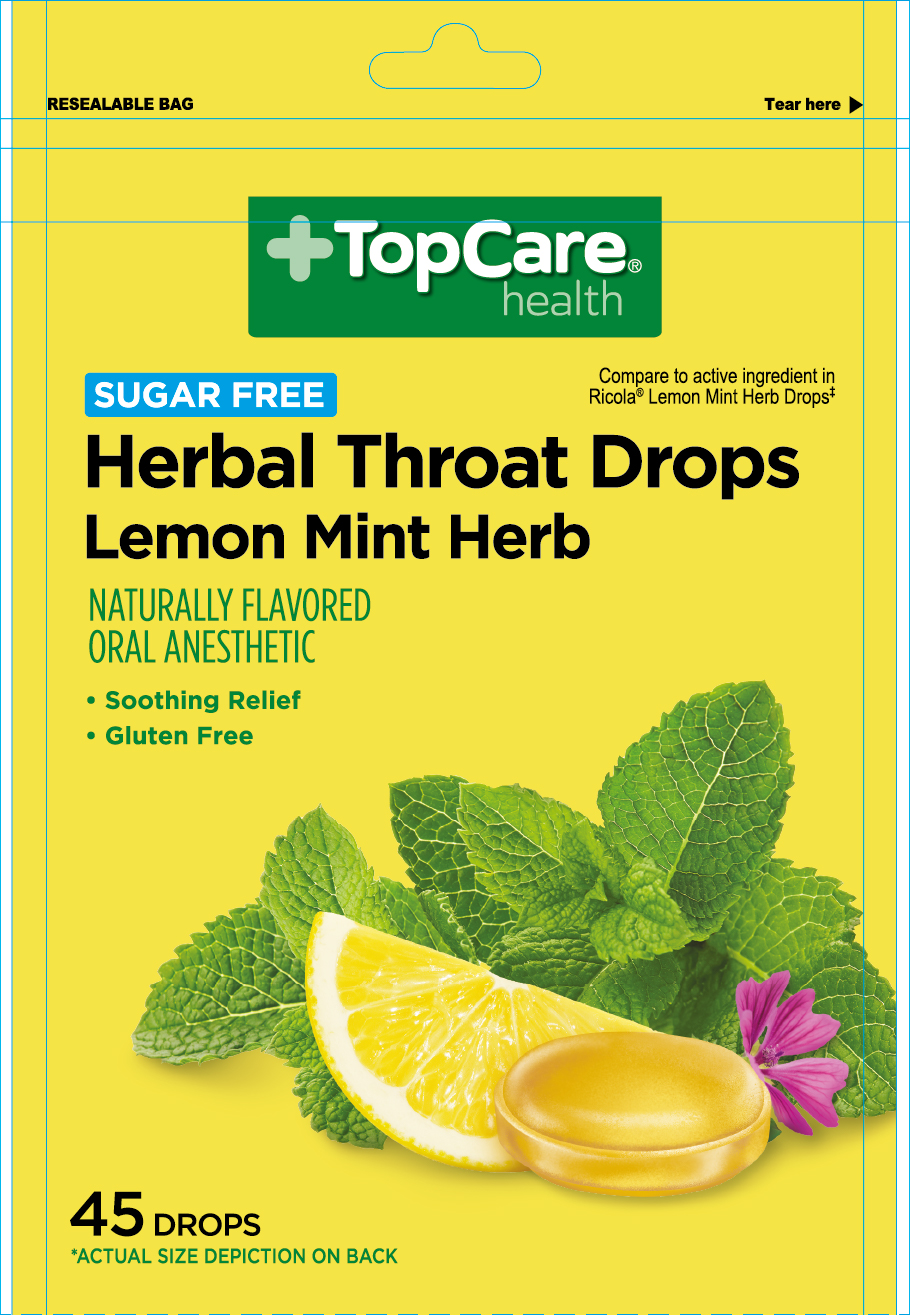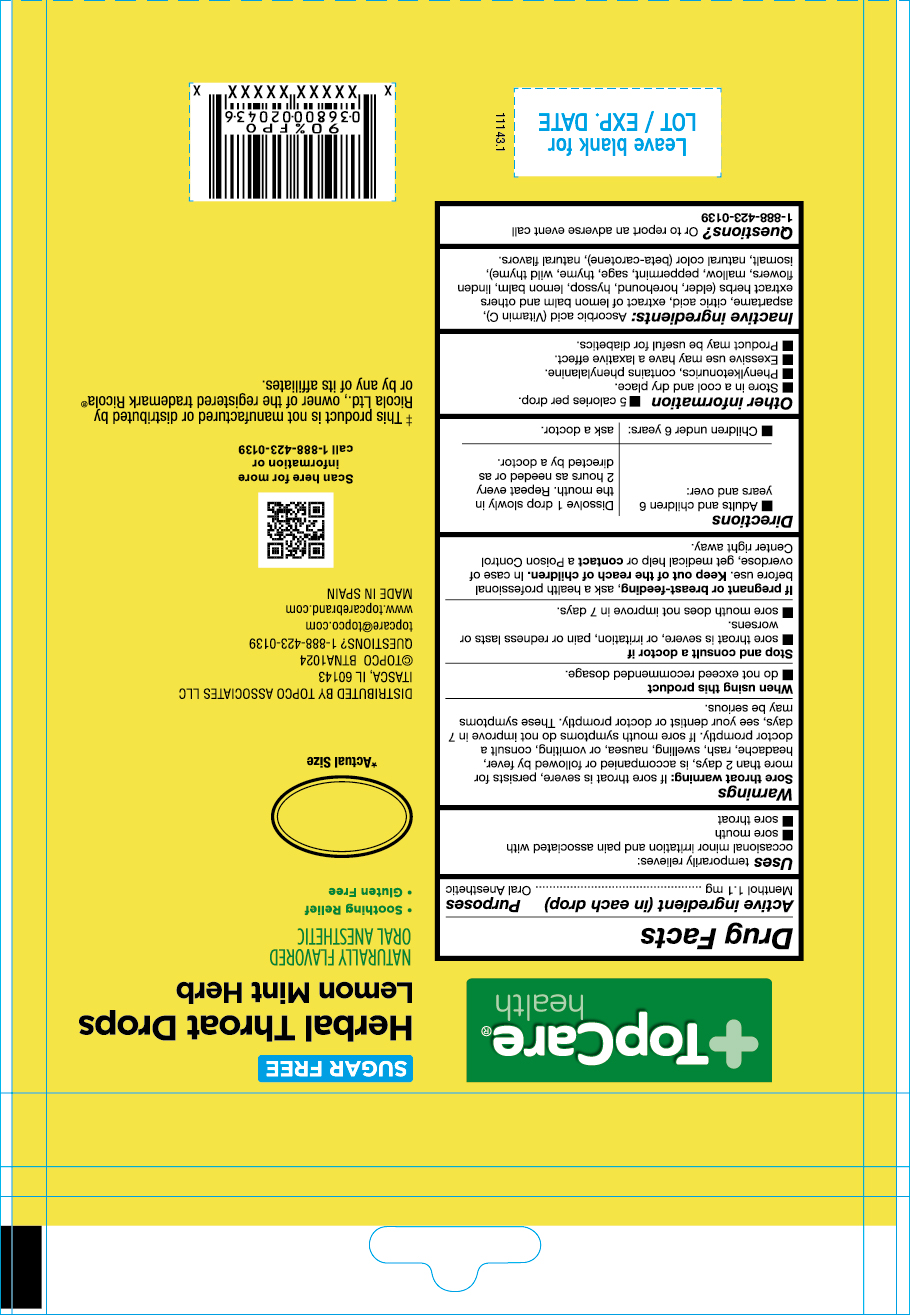 DRUG LABEL: Herbal Throat Drops Lemon Mint Herb
NDC: 76162-060 | Form: PASTILLE
Manufacturer: Topco Associates LLC
Category: otc | Type: HUMAN OTC DRUG LABEL
Date: 20250305

ACTIVE INGREDIENTS: MENTHOL 1.1 mg/1 1
INACTIVE INGREDIENTS: LEMON BALM OIL; THYME; ISOMALT; BETA CAROTENE; FLAVONE; ASCORBIC ACID; CITRIC ACID; TILIA CORDATA FLOWER; MALVA NEGLECTA WHOLE; WILD THYME; PEPPERMINT; SAGE; ASPARTAME; SAMBUCUS NIGRA FLOWER; HYSSOPUS OFFICINALIS WHOLE; HOREHOUND

USES

Uses temporarily relieves:

ocassional minor irrititation and pain associated with

- sore mouth
- sore throat

Stop and Consult a Doctor if

- sore throat is severe, or irritation, pain or redness lasts or worsens
- sore mouth does not improve in 7 days.

If pregnant or breast feeding, ask a health professional before use.

Keep out of the reach of children

Keep out of the reach of chilcren. In case of overdose, get medical help or contact a Poison Control Center right away.

Questions?

Questions? or to report an adverse event call 1-888-423-0139

When using this product

- do not exceed recomended dosage

Other information

- 5 calories per drop
- Store in a cool and dry place
- Phenylketonurics contains phenylalanine
- Excessive use may have a laxative effect
- Product may be useful for diabetics

Warnings

Sore throat warning: If sore throat is severe, persists for more than 2 days, is accompanied or followed by fever, headache, rash, swelling, nausea, or vomiting, consult a doctor promptly. If sore mouth symptons do not improve in 7 days, see your dentist or doctor promptly. These symptons may be serious

Inactive Ingredients

Ascorbic acid,Citric acid, Elderflower, Horehound, Hyssop, Lemon balm, Linden flowers, Mallow, Peppermint, Sage, Thyme, Wild thyme, Aspartame, Isomalt, Betacarotene, Natural flavors

Directions

- Adults and children 6 years and over: dissolve 1 drop slowly in the mouth. Repeat every 2 hours as needed or as directed by the doctor
- Children under 6 years: as a doctor

Indications & Usage Section

Uses temporarily relieves:

ocassional minor irritation and pain associated with

- sore mouth
- sore throat